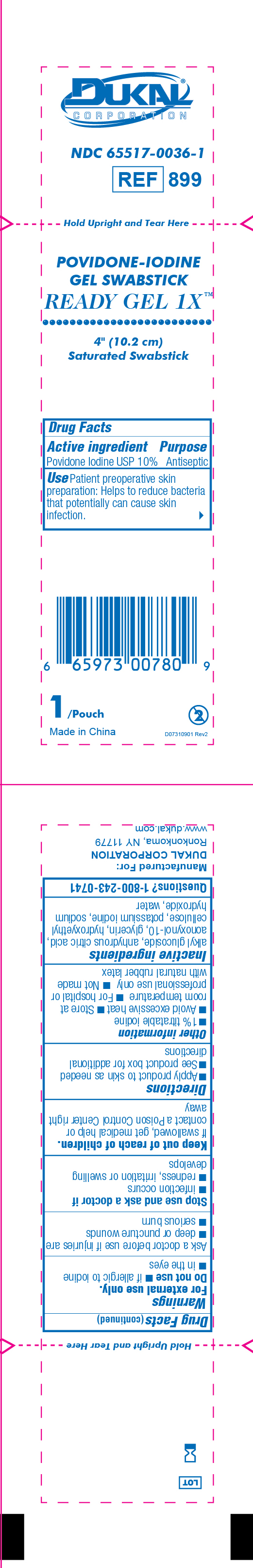 DRUG LABEL: Povidone-Iodine Gel Swabstick
NDC: 65517-0036 | Form: GEL
Manufacturer: Dukal LLC
Category: otc | Type: HUMAN OTC DRUG LABEL
Date: 20251119

ACTIVE INGREDIENTS: POVIDONE-IODINE 10 mg/1 g
INACTIVE INGREDIENTS: WATER; HYDROXYETHYL CELLULOSE (5000 CPS AT 1%); POTASSIUM IODIDE; GLYCERIN; ANHYDROUS CITRIC ACID; SODIUM HYDROXIDE; NONOXYNOL-10

Active Ingredient

Povidone-Iodine USP 10%

Purpose

Antispetic

Use

Antiseptic Skin Preparation

Warnings

For External Use Only

Do not use

- If allergic to Iodine
- in the eyes

Ask a doctor before use if injuries are

- deep or puncture wounds
- Serious burn

Stop use and ask doctor if

- infection occurs
- redness, irritation or swelling develops

Keep out of reach of children

If swallowed, get medical help or contact Poison Control Center right away

Directions

- apply product to skin as needed
- see product box for additional directions

Other Information

- 1% titratable iodine
- Avoid excessive heat
- Store at room temperature
- For hospital or professional use only
- Not made with natural rubber latex

Inactive Ingredients

alkyl glucoside, anhydrous citric acid, aonoxynol-10, glycerin, hydroxyethyl cellulose, potassium iodine, sodium hydroxide, water

Dukal Povidone-Iodine Gel Swabstick

DUKAL™
CORPORATION

NDC 65517-0036-1

REF 899

Hold Upright and Tear Here

POVIDONE-IODINE

Gel Swabstick

Ready Gel 1X™

4" (10.2cm)

Saturated Swabstick

Drug Facts

Active ingredients Purpose
Povidone Iodine USP 10% Antiseptic

Use Patient preoperative skin preparation: Helps to

reduce bacterial that potentially can cause skin infection

1/Pouch 2

Made in China D07310901 Rev2